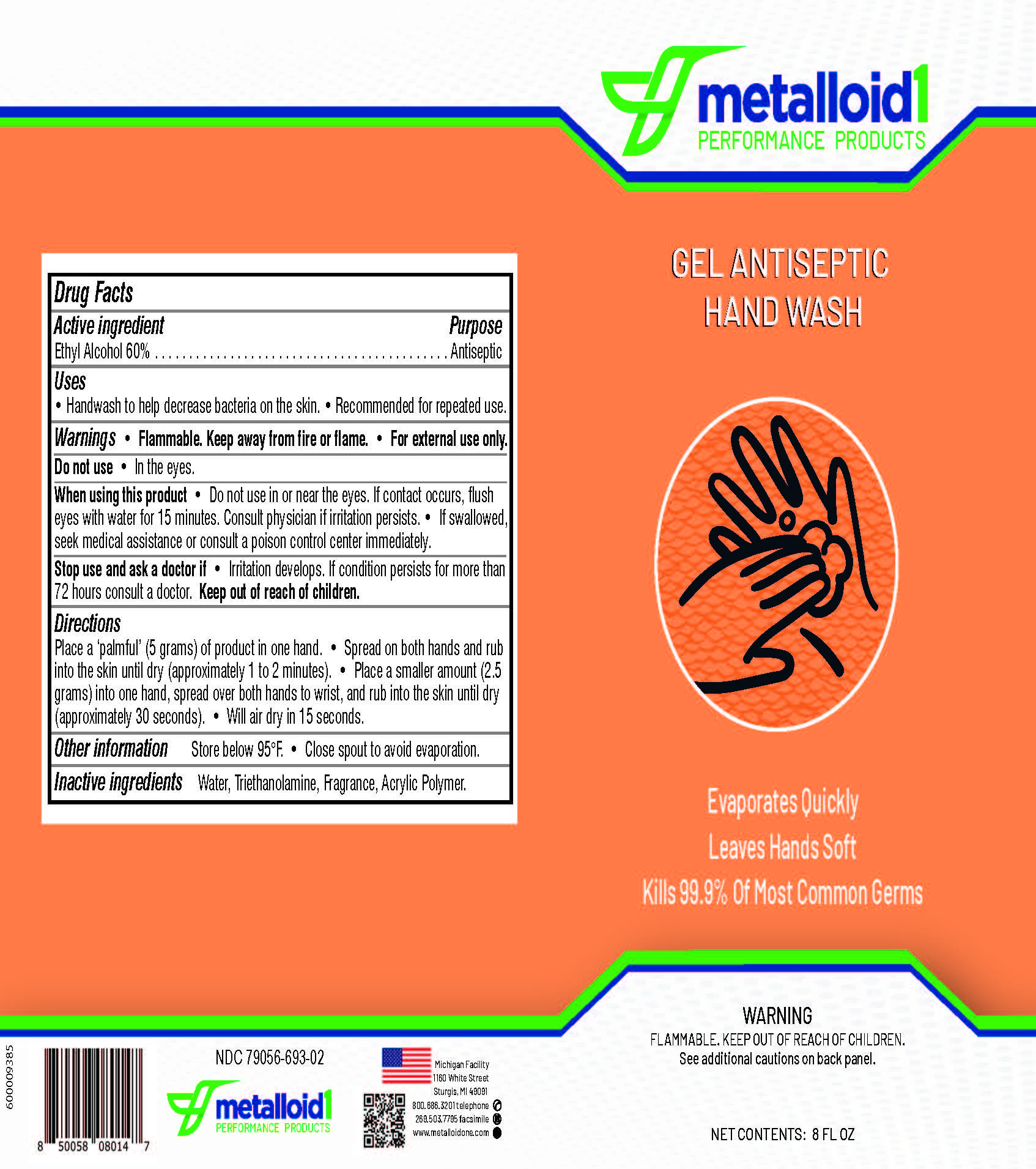 DRUG LABEL: Gel Antiseptic Hand Wash
NDC: 79056-693 | Form: LIQUID
Manufacturer: Metalloid Corporation
Category: otc | Type: HUMAN OTC DRUG LABEL
Date: 20250909

ACTIVE INGREDIENTS: ALCOHOL 67 mL/100 mL
INACTIVE INGREDIENTS: CARBOMER 940; TROLAMINE; WATER

Hand Sanitizer PLD template II

Active Ingredient

Ethyl Alcohol 60%..........Antiseptic

purpose

Antiseptic

Uses

- Handwash to help decrease bacterial on the skin.
- Recommended for repeated use.

Warnings

- Flammable. Keep away from fire or flame.
- For external use only.

do not use

- In the eyes

When Using

- Do not use in or near the eyes.
- If contact occurs, flush eyes with water for 15 minutes. Consult physician if irritation persists.
- If swallowed, seek medical assistance or consult a poison control center immediately.

Stop Use

- Stop use and ask a doctor if: Irritation develops. If condition persists for more than 72 hours consult a doctor.
- Keep out of reach of children.

- Keep out of reach of children.

Directions for Use

- Place a palmful (5 grams) of product in one hand,.
- Spread on both hands and rub into the skin until dry (approximately 1 to 2 minutes).
- Place a smaller amount (2.5 grams) into one hand, spread over both hands to wrist and rub into the skin until dry (approximately 30 seconds).
- Will air dry in 15 seconds.

OTHER SAFETY INFORMATION

- Store below 95o F.
- Close spout to avoid evaporation.

INACTIVE INGREDIENT

Water, triethanolamine, fragrance, acrylic polymer